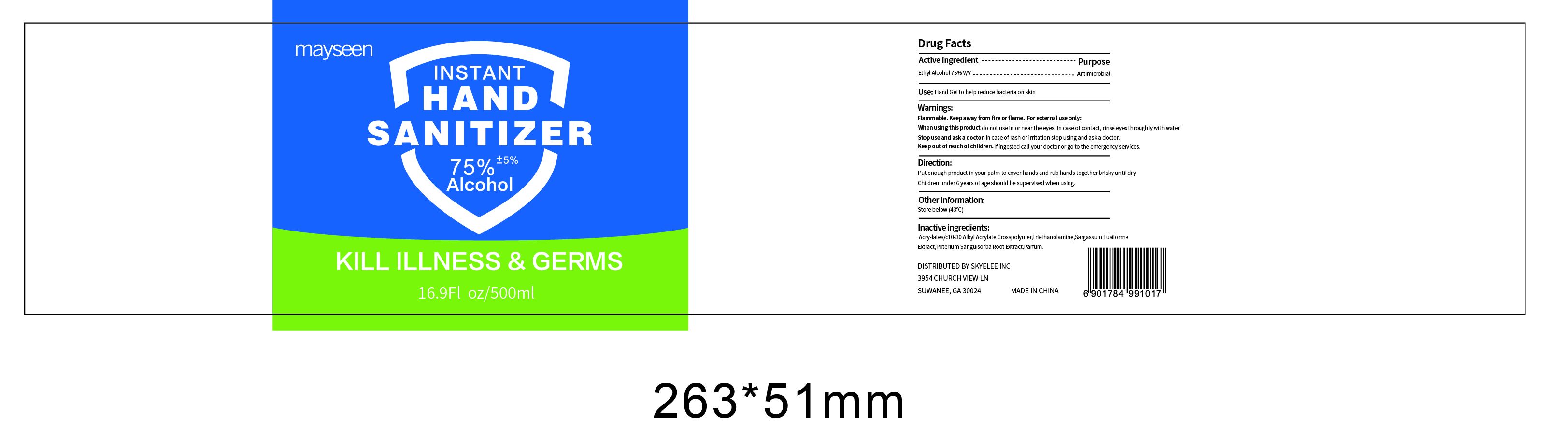 DRUG LABEL: Hand Sanitizer
NDC: 78565-016 | Form: GEL
Manufacturer: Meixin Beauty & Health Care Products Co., Ltd.
Category: otc | Type: HUMAN OTC DRUG LABEL
Date: 20200907

ACTIVE INGREDIENTS: ALCOHOL 75 mL/100 mL
INACTIVE INGREDIENTS: FRAGRANCE CLEAN ORC0600327; SARGASSUM FUSIFORME; SANGUISORBA MINOR ROOT; CARBOMER INTERPOLYMER TYPE A (55000 CPS); TROLAMINE

78565-016
Hand Sanitizer

Active Ingredient(s)

Ethyl Alcohol 75% v/v

Purpose

Antimicrobial

INDICATIONS AND USAGE

Hand sanitizer to help reduce bacteria on skin.

Warnings

Flammable. Keep away from fire or flame.
For external use only.

When using this product do not use in or near the eyes.
In case of contact, rinse eyes thoroughly with water.

Stop use and ask a doctor in case of rash or irritation stop using and ask a doctor.

Keep out of reach of chlldren.if ingested call your doctor or go to the emergency services.

do not use in or near the eyes.

When using this product do not use in or near the eyes.
In case of contact, rinse eyes thoroughly with water.

Stop use and ask a doctor in case of rash or irritation stop using and ask a doctor.

Keep out of reach of chlldren.if ingested call your doctor or go to the emergency services.

Stop use and ask a doctor in case of rash or irritation stop using and ask a doctor.

KEEP OUT OF REACH OF CHILDREN

Keep out of reach of chlldren.if ingested call your doctor or go to the emergency services.

Directions

Put enough product in your palm to cover hands and rubands together brisky until dry.
Children under 6 years of age should be supervised when using.

Other information

Store below(43°C)

Inactive ingredients

Acry-lates/c10-30 Alkyl Acrylate crosspolymer, Triethanolamine,Sargassum Fusiforme Extract,Poterium Sanguisorba Root Extract,Parfum.